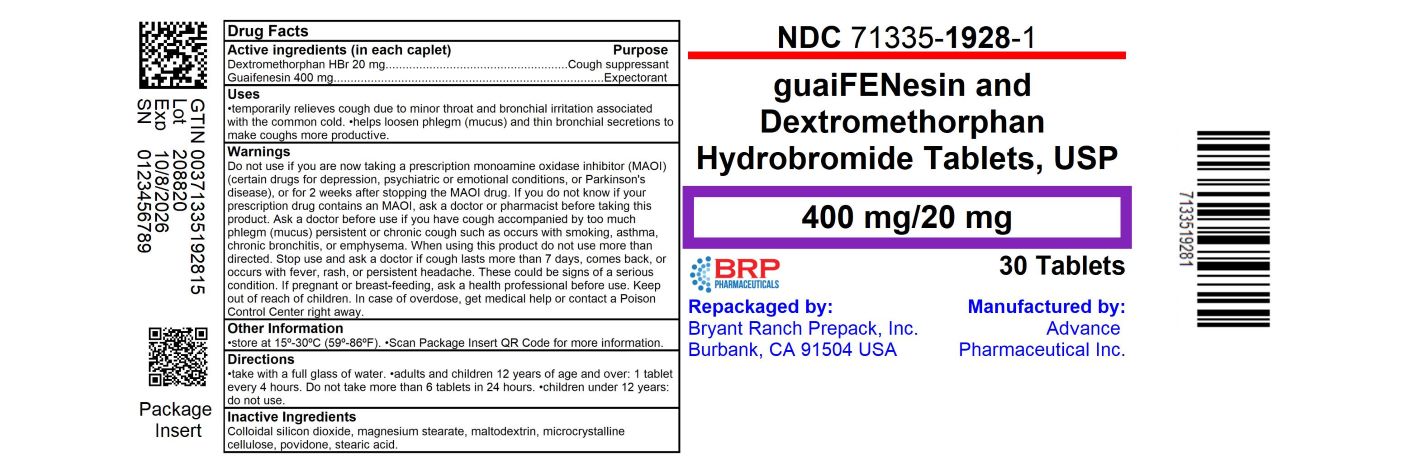 DRUG LABEL: Mucus Relief Cough and Congestion DM
NDC: 71335-1928 | Form: TABLET
Manufacturer: Bryant Ranch Prepack
Category: otc | Type: HUMAN OTC DRUG LABEL
Date: 20241008

ACTIVE INGREDIENTS: DEXTROMETHORPHAN HYDROBROMIDE 20 mg/1 1; GUAIFENESIN 400 mg/1 1
INACTIVE INGREDIENTS: MAGNESIUM STEARATE; MALTODEXTRIN; POVIDONE, UNSPECIFIED; SILICON DIOXIDE; STEARIC ACID; MICROCRYSTALLINE CELLULOSE

Guaifenesin 400 mg - DextromethorphanCaplets 20 mg Caplets

Active ingredients (in each caplet)

Dextromethorphan HBr 20 mg
Guaifenesin 400 mg

Purpose

Cough suppressant
Expectorant

Uses

- temporarily relieves cough due to minor throat and bronchial irritation associated with the common cold
- helps loosen phlegm (mucus) and thin bronchial secretions to make coughs more productive

Warnings

Do not use

if you are now taking a prescription monoamine oxidase inhibitor (MAOI) (certain drugs for depression, psychiatric or emotional conditions, or Parkinson's disease), or for 2 weeks after stopping the MAOI drug. If you do not know if your prescription drug contains an MAOI, ask a doctor or pharmacist before taking this product.

Ask a doctor before use if you have

- cough accompanied by too much phlegm (mucus)
- persistent or chronic cough such as occurs with smoking, asthma, chronic bronchitis, or emphysema

When using this product

do not use more than directed.

Stop use and ask a doctor if

cough lasts more than 7 days, comes back, or occurs with fever, rash, or persistent headache. These could be signs of a serious condition.

If pregnant or breast-feeding,

ask a health professional before use.

Keep out of reach of children.

In case of overdose, get medical help or contact a Poison Control Center right away.

Directions

- take with a full glass of water
- adults and children 12 years of age and over: 1 tablet every 4 hours. Do not take more than 6 tablets in 24 hours.
- children under 12 years: do not use

Other information

- store at 15º-30ºC (59º-86ºF)

Inactive ingredients

Colloidal silicon dioxide, magnesium stearate, maltodextrin, microcrystalline cellulose, povidone, stearic acid

Questions or comments?

call 804-270-4498, 8.30 am-4.30 pm ET, Monday - Friday
TAMPER EVIDENT: DO NOT USE IF IMPRINTED SAFETY SEAL UNDER CAP IS BROKEN OR MISSING

HOW SUPPLIED

Guaifenesin and Dextromethorphan HBr 400 mg/20 mg Tablets

- NDC: 71335-1928-1: 30 Tablets in a BOTTLE
- NDC: 71335-1928-2: 20 Tablets in a BOTTLE
- NDC: 71335-1928-3: 18 Tablets in a BOTTLE

store at 15º-30ºC (59º-86ºF)

Repackaged/Relabeled by:
Bryant Ranch Prepack, Inc.
Burbank, CA 91504

PACKAGE LABEL

Guaifenesin and Dextromethorphan HBr 400 mg/20 mg Tablets